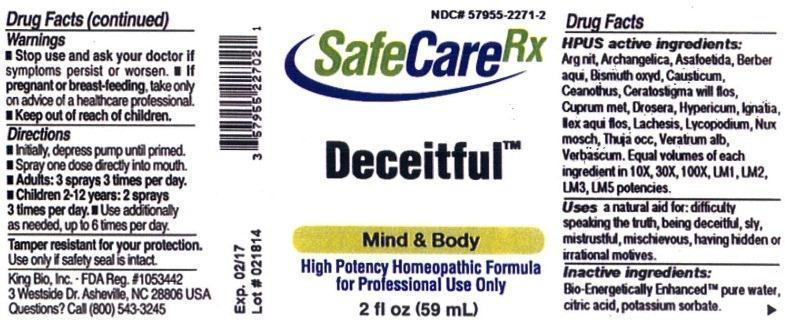 DRUG LABEL: Deceitful
NDC: 57955-2271 | Form: LIQUID
Manufacturer: King Bio Inc.
Category: homeopathic | Type: HUMAN OTC DRUG LABEL
Date: 20140331

ACTIVE INGREDIENTS: SILVER 10 [hp_X]/59 mL; ANGELICA ARCHANGELICA ROOT 10 [hp_X]/59 mL; ASAFETIDA 10 [hp_X]/59 mL; MAHONIA AQUIFOLIUM ROOT BARK 10 [hp_X]/59 mL; BISMUTH OXIDE 10 [hp_X]/59 mL; CAUSTICUM 10 [hp_X]/59 mL; CEANOTHUS AMERICANUS LEAF 10 [hp_X]/59 mL; CERATOSTIGMA WILLMOTTIANUM FLOWER 10 [hp_X]/59 mL; COPPER 10 [hp_X]/59 mL; DROSERA ROTUNDIFOLIA 10 [hp_X]/59 mL; HYPERICUM PERFORATUM 10 [hp_X]/59 mL; STRYCHNOS IGNATII SEED 10 [hp_X]/59 mL; ILEX AQUIFOLIUM FLOWERING TOP 10 [hp_X]/59 mL; LACHESIS MUTA VENOM 10 [hp_X]/59 mL; LYCOPODIUM CLAVATUM SPORE 10 [hp_X]/59 mL; NUTMEG 10 [hp_X]/59 mL; THUJA OCCIDENTALIS LEAFY TWIG 10 [hp_X]/59 mL; VERATRUM ALBUM ROOT 10 [hp_X]/59 mL; VERBASCUM THAPSUS 10 [hp_X]/59 mL
INACTIVE INGREDIENTS: WATER; CITRIC ACID MONOHYDRATE; POTASSIUM SORBATE

Deceitful™

Drug Facts

____________________________________________________________________________________________________________________

HPUS active ingredients: Argentum metallicum, Angelica archangelica, Asafoetida, Berberis aquifolium, Bismuthum oxydatum, Causticum, Ceanothus americanus, Ceratostigma willmottianum, flos, Cuprum metallicum, Drosera, Hypericum perforatum, Ignatia amara, Ilex aquifolium, flos, Lachesis mutus, Lycopodium clavatum, Nux moschata, Thuja occidentalis, Veratrum album, Verbascum thapsus. Equal volumes of each ingredient in 10X, 30X, 100X, LM1, LM2, LM3, LM5 potencies.

INDICATIONS AND USAGE

Uses a natural aid for: difficulty speaking the truth, being deceitful, sly, mistrustful, mischievous, having hidden or irrational motives.

INACTIVE INGREDIENT

Inactive ingredients: Bio-Energetically Enhanced pure water, citric acid, potassium sorbate.

Warnings

- Stop use and ask your doctor if symptoms persist or worsen.
- If pregnant or breast-feeding, take only on advice of a healthcare professional.

- Keep out of reach of children.

Directions:

- Initially, depress pump until primed.
- Spray one dose directly into mouth.
- Adults: 3 sprays 3 times per day.
- Children 2-12 years: 2 sprays 3 times per day.
- Use additionally as needed, up to 6 times per day.

OTHER SAFETY INFORMATION

Tamper resistant for your protection. Use only if safety seal is intact.

PURPOSE

Uses a natural aid for:

- difficulty speaking the truth
- being deceitful
- sly
- mistrustful
- mischievous
- having hidden
- irrational motives